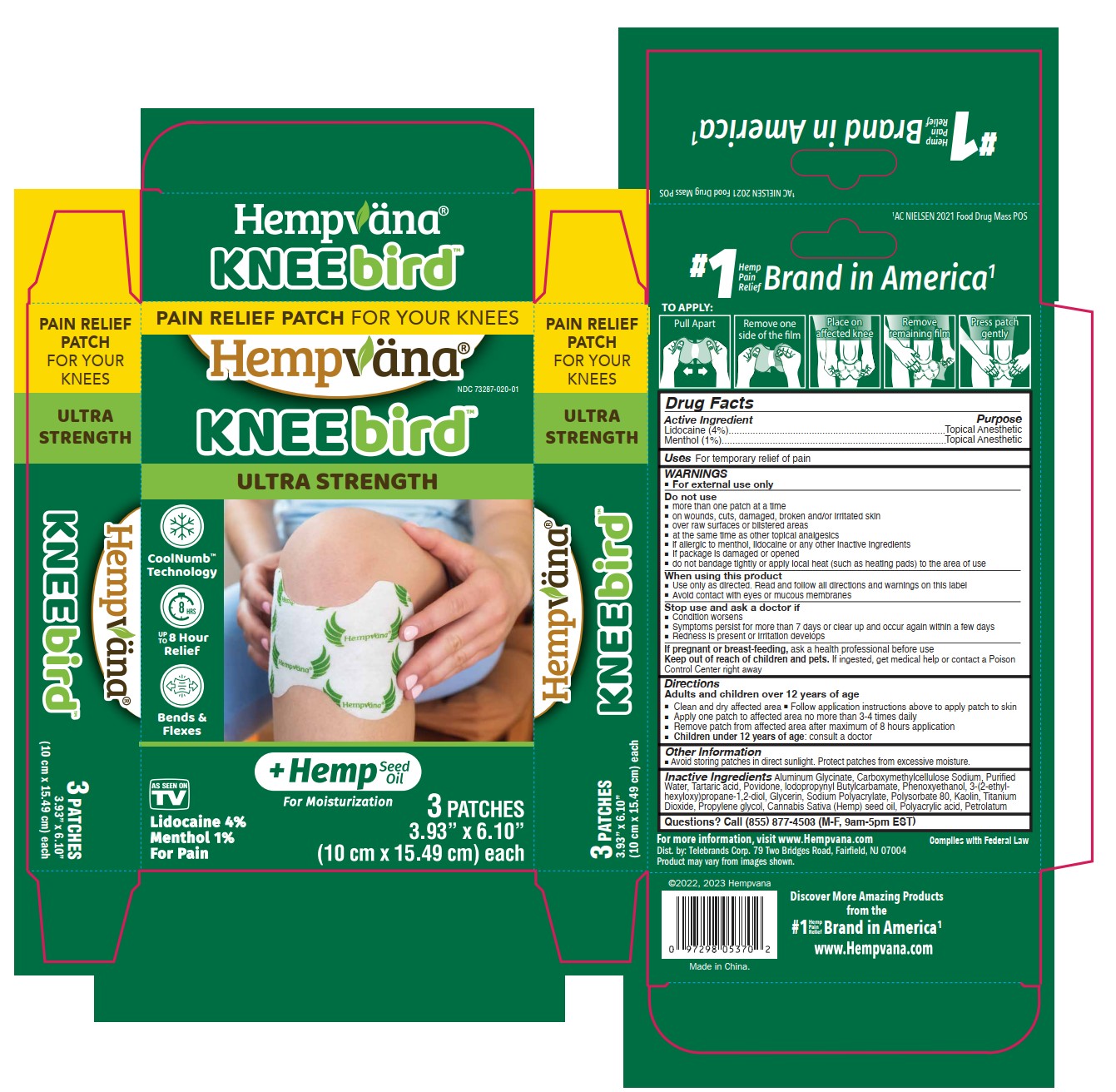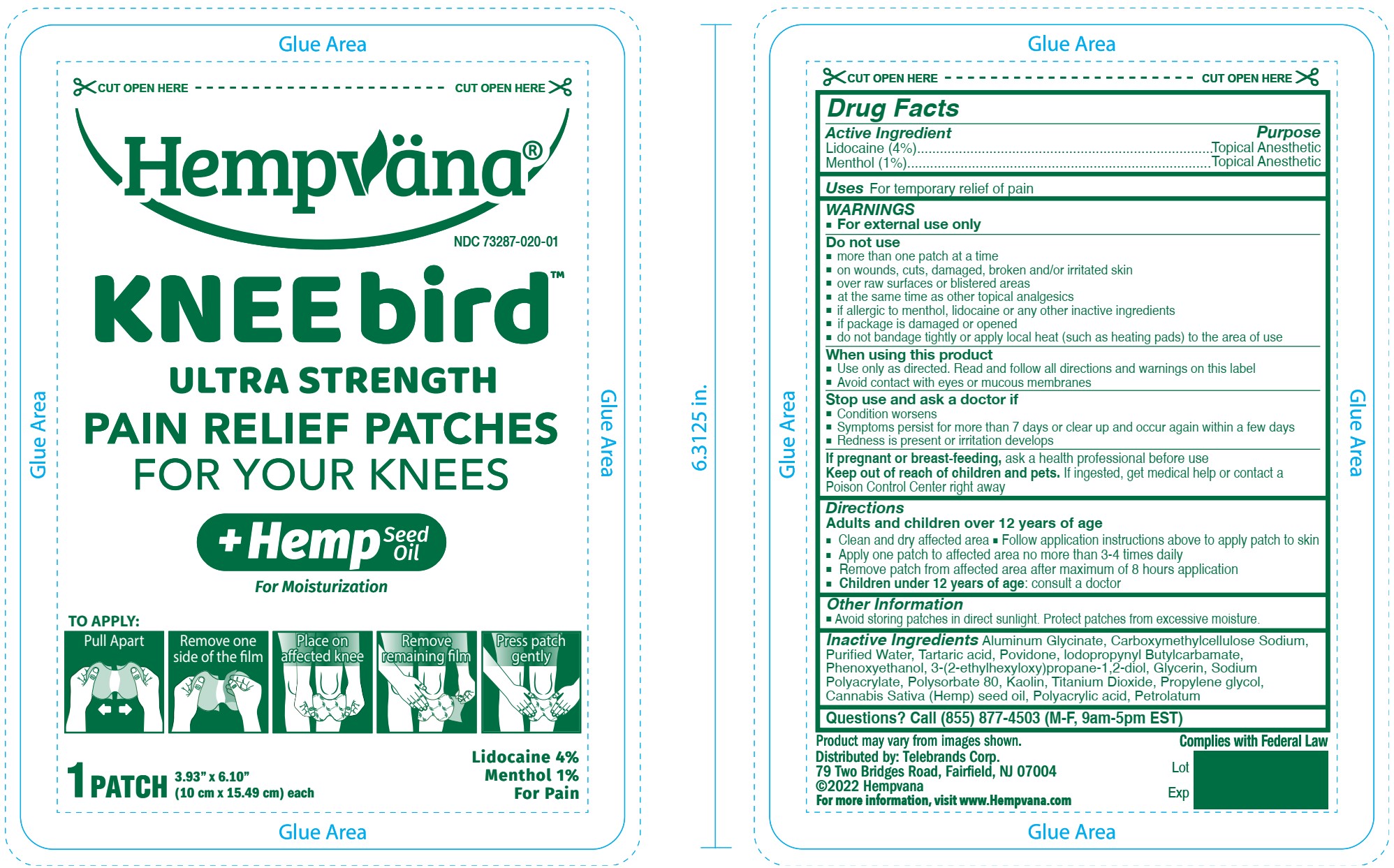 DRUG LABEL: Hempvana Knee Bird Ultra Strength Pain Relief
NDC: 73287-020 | Form: PATCH
Manufacturer: TELEBRANDS CORP
Category: otc | Type: HUMAN OTC DRUG LABEL
Date: 20241120

ACTIVE INGREDIENTS: MENTHOL 1 g/100 g; LIDOCAINE 4 g/100 g
INACTIVE INGREDIENTS: DIHYDROXYALUMINUM AMINOACETATE ANHYDROUS; KAOLIN; POVIDONE; CARBOXYMETHYLCELLULOSE SODIUM; GLYCERIN; SODIUM POLYACRYLATE (2500000 MW); CANNABIS SATIVA SEED OIL; POLYACRYLIC ACID (250000 MW); IODOPROPYNYL BUTYLCARBAMATE; TITANIUM DIOXIDE; POLYSORBATE 80; WATER; PROPYLENE GLYCOL; TARTARIC ACID; ETHYLHEXYLGLYCERIN; PHENOXYETHANOL; PETROLATUM

Hempvana Knee Bird Ultra Strength Pain Relief Patches

Active ingredients

Lidocaine (4%)

Menthol (1%)

Purpose

Lidocaine (4%)..................Topical Anesthetic

Menthol (1%)....................Topical Anesthetic

Uses

For temporary relief of pain

Warnings

For external use only

Do not use

- more than one patch at a time
- on wounds, cuts, damaged, broken and/or irritated skin
- over raw surfaces or blistered areas
- at the same time as other topical analgesics
- if allergic to menthol, lidocaine or any other inactive ingredients
- if package is damaged or opened
- do not bandage tightly or apply local heat (such as heating pads) to the area of use

When using this product

- Use only as directed. Read and follow all directions and warnings on this label
- Avoid contact with eyes or mucous membranes

Stop use and ask a doctor if

- Condition worsens
- Symptoms persist for more than 7 days or clear up and occur again within a few days
- Redness is present or irritation develops

PREGNANCY OR BREAST FEEDING

If pregnant or breast-feeding,ask a health professional before use

Keep out of reach of children and pets.If ingested, get medical help or contact a Poison Control Center right away

Directions

Adults and children over 12 years of age

- Clean and dry affected area
- Follow application instructions above to apply patch to skin
- Apply one patch to affected area no more than 3-4 times daily
- Remove patch from affected area after maximum of 8 hours application
- Children under 12 years of age:consult a doctor

Other information

- Avoid storing patches in direct sunlight. Protect patches from excessive moisture.

Inactive ingredients

Aluminum Glycinate, Carboxymethylcellulose Sodium, Purified Water, Tartaric acid, Povidone, Iodopropynyl Butylcarbamate, Phenoxyethanol, 3-(2-ethylhexyloxy)propane-1,2-diol, Glycerin, Sodium Polyacrylate, Polysorbate 80, Kaolin, Titanium Dioxide, Propylene Glycol, Cannabis Sativa (Hemp) Seed Oil, Polyacrylic acid, Petrolatum

Questions?

Call (855) 877-4503 (M-F, 9am-5pm EST)

PACKAGE LABEL

Pain Relief Patch For Your Knees

Hempvana

KNEEbird

Ultra Strength

CoolNumb Technology

Up to 8 Hour Relief

Bends & Flexes

As Seen on TV

+Hemp Seed Oil For Moisturization

Lidocaine 4%

Menthol 1%

For Pain

3 Patches

3.93"x6.10"

(10 cm x 15.49 cm) each